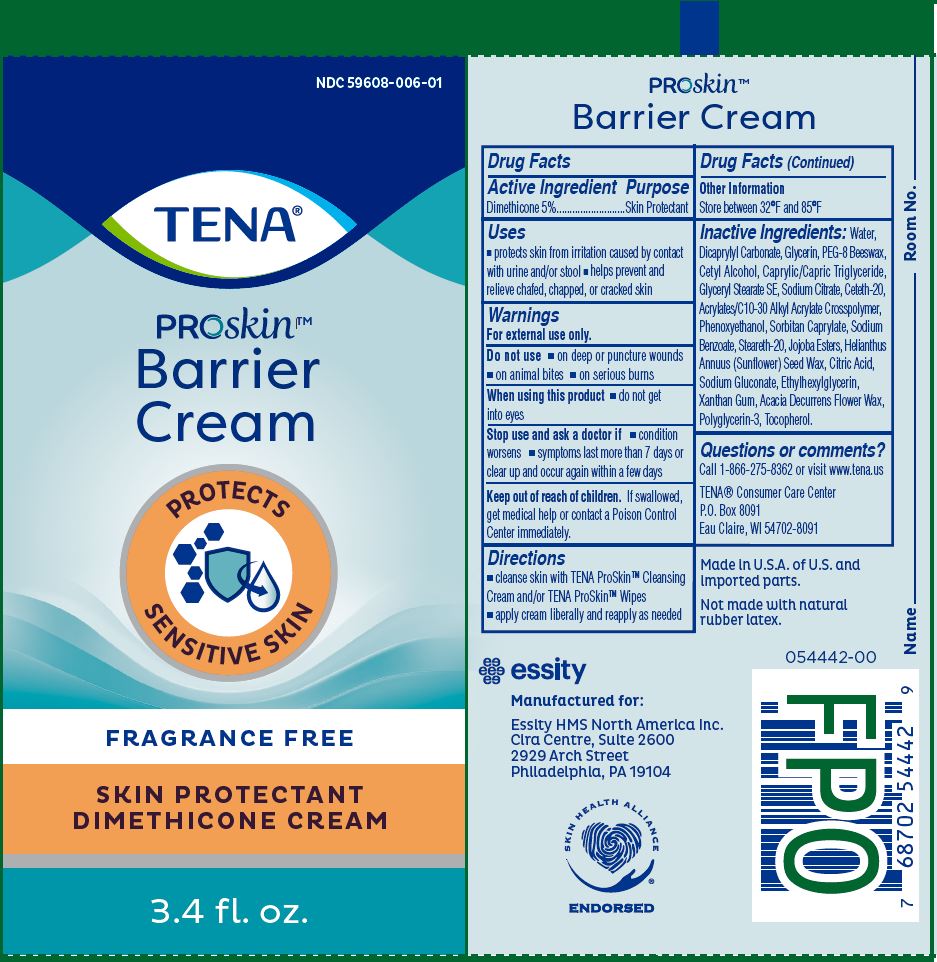 DRUG LABEL: TENA PROSKIN BARRIER
NDC: 59608-006 | Form: CREAM
Manufacturer: Essity HMS North America Inc
Category: otc | Type: HUMAN OTC DRUG LABEL
Date: 20251221

ACTIVE INGREDIENTS: DIMETHICONE 5 g/100 mL
INACTIVE INGREDIENTS: WATER; DICAPRYLYL CARBONATE; GLYCERIN; PEG-8 BEESWAX; CETYL ALCOHOL; MEDIUM-CHAIN TRIGLYCERIDES; GLYCERYL STEARATE SE; SODIUM CITRATE; CETETH-20; CARBOMER COPOLYMER TYPE A (ALLYL PENTAERYTHRITOL CROSSLINKED); PHENOXYETHANOL; SORBITAN MONOCAPRYLATE; SODIUM BENZOATE; STEARETH-20; HYDROGENATED JOJOBA OIL/JOJOBA OIL, RANDOMIZED (IODINE VALUE 40-44); HELIANTHUS ANNUUS SEED WAX; ANHYDROUS CITRIC ACID; SODIUM GLUCONATE; ETHYLHEXYLGLYCERIN; XANTHAN GUM; ACACIA DECURRENS FLOWER WAX; POLYGLYCERIN-3; TOCOPHEROL

Essity (as PLD) - TENA PROSKIN BARRIER CREAM (59608-006)

ACTIVE INGREDIENT

Dimethicone 5%

PURPOSE

Skin Protectant

USES

- protects skin from irritation casued by contact with urine and/or stool
- helps prevent and releive chafed, chapped, or cracked skin

WARNINGS

For external use only.

Do not use

- on deep or puncture wounds
- on animal bites
- on serious burns

When using this product

- do not get into eyes

Stop use and ask a doctor if

- condition worsens
- symptoms last more than 7 days or clear up and occur again within a few days

Keep out of reach of children. If swallowed, get medical help or contact a Poison Control Center immediately.

DIRECTIONS

- cleanse skin with TENA PROSKIN Cleansing Cream and/or TENA PROSKIN WIPES
- apply cream liberally and reapply as needed

OTHER INFORMATION

Store between 32°F and 85°F

INACTIVE INGREDIENTS

Water, Dicaprylyl Carbonate, Glycerin, PEG-8 Beeswax, Cetyl Alcohol, Caprylic/Capric Triglyceride, Glyceryl Stearate SE, Sodium Citrate, Ceteth-20, Acrylates/C10-30 Alkyl Acrylate Crosspolymer, Phenoxyethanol, Sorbitan Caprylate, Sodium Benzoate, Steareth-20, Jojoba Esters, Helianthus Annuus (Sunflower) Seed Wax, Citric Acid, Sodium Gluconate, Ethylhexylglycerin, Xanthan Gum, Acacia Decurrens Flower Wax,
Polyglycerin-3, Tocopherol.

QUESTIONS OR COMMENTS?

Call 1-800-992-9939 or visit www.tena.us

TENA® Consumer Care Center
P.O. Box 8091
Eau Claire, WI 54702-8091